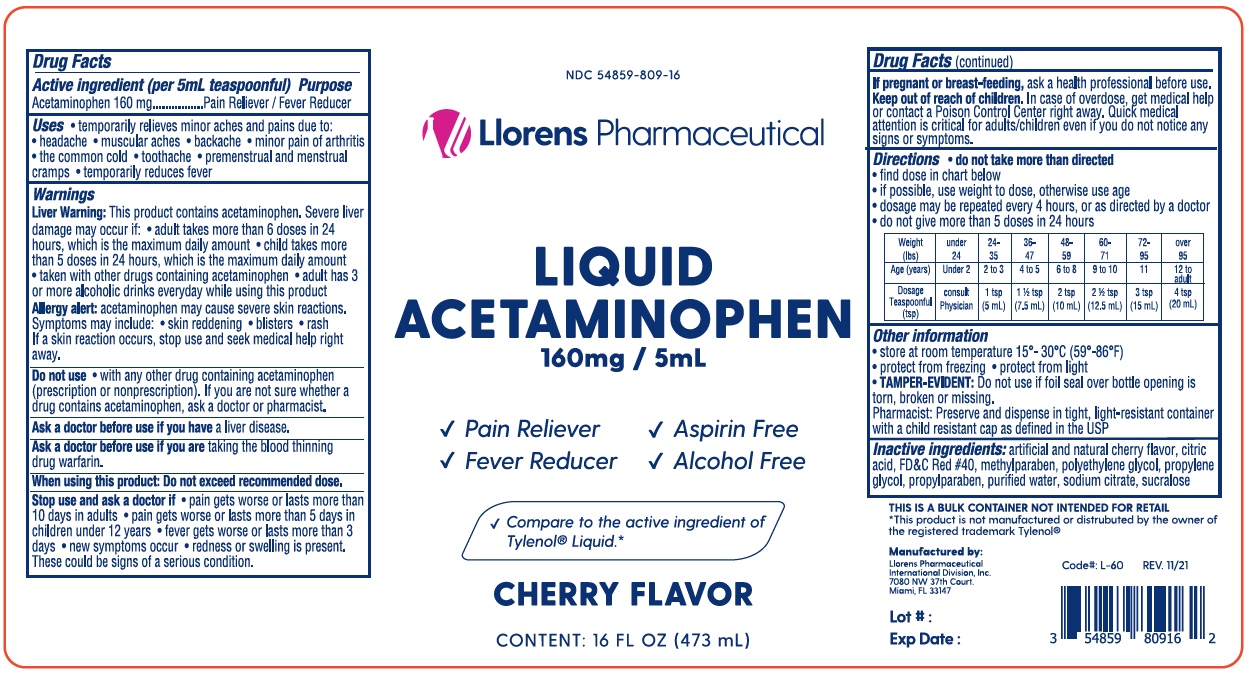 DRUG LABEL: Liquid Acetaminophen
NDC: 54859-809 | Form: LIQUID
Manufacturer: LLORENS PHARMACEUTICALS INTERNATIONAL DIVISION
Category: otc | Type: HUMAN OTC DRUG LABEL
Date: 20251231

ACTIVE INGREDIENTS: ACETAMINOPHEN 160 mg/5 mL
INACTIVE INGREDIENTS: ANHYDROUS CITRIC ACID; FD&C RED NO. 40; METHYLPARABEN; POLYETHYLENE GLYCOL, UNSPECIFIED; PROPYLENE GLYCOL; PROPYLPARABEN; WATER; SODIUM CITRATE; SUCRALOSE

Llorens- Liquid Acetaminophen 809

Active ingredient (per 5 mL teaspoonful)

Acetaminophen 160 mg

Purpose

Pain Reliever/Fever Reducer

Uses

- temporarily relieves minor aches and pains due to:
- headache
- muscular aches
- backache
- minor pain of arthritis
- the common cold
- toothache
- premenstrual and menstrual cramps
- temporarily reduces fever

Warnings

Liver Warning: This product contains acetaminophen. Severe liver damage may occur if:

- adult takes more than 6 doses in 24 hours, which is the maximum daily amount
- child takes more than 5 doses in 24 hours, which is the maximum daily amount
- taken with other drugs containing acetaminophen
- adult has 3 or more alcoholic drinks everyday while using this product

Allergy alert: acetaminophen may cause severe skin reactions. Symptoms may include:

- skin reddening
- blisters
- rash

If a skin reaction occurs, stop use and seek medical help right away.

Do not use with any other drug containing acetaminophen (prescription or nonprescription). If you are not sure whether a drug contains acetaminophen, ask a doctor or pharmacist.

Ask a doctor before use if you have liver disease.

Ask a doctor before use if you are taking the blood thinning drug warfarin.

When using this product: Do not exceed recommended dose.

Stop use and ask a doctor if

- pain gets worse or lasts more than 10 days in adults
- pain gets worse or lasts more than 5 days in children under 12 years
- fever gets worse or lasts more than 3 days
- new symptoms occur
- redness or swelling is present. These could be signs of a serious condition.

PREGNANCY OR BREAST FEEDING

If pregnant or breast-feeding, ask a health professional before use

Keep out of reach of children. In case of overdose, get medical help or contact a Paoison Control Center right away. Quick medical attention is critical for adults/children even if you do not notice any signs or symptoms.

Directions

- do not take more than directed
- find dose in chart below
- if possible, use weight to dose, otherwise use age
- dosage may be repeasted every 4 hours, or as directed by a doctor
- do not give more than 5 doses in 24 hours

Weight (lbs) | under 24 | 24-35 | 36-47 | 48-59 | 60-71 | 72-95 | over 95
Age (years) | under 2 | 2 to 3 | 4 to 5 | 6 to 8 | 9 to 10 | 11 | 12 to adult
Dosage Teaspoonful (tsp) | consult Physician | 1 tsp (5 mL) | 1 1/2 tsp (7.5 mL) | 2 tsp (10 mL) | 2 1/2 tsp (12.5 mL) | 3 tsp (15 mL) | 4 tsp (20 mL)

INACTIVE INGREDIENT

Inactive ingredients: artificial and natural cherry flavor, citric acid, FD&C Red #40, methylparaben, polyethylene glycol, propylene glycol, propylparaben, purified water, sodium citrate, sucralose